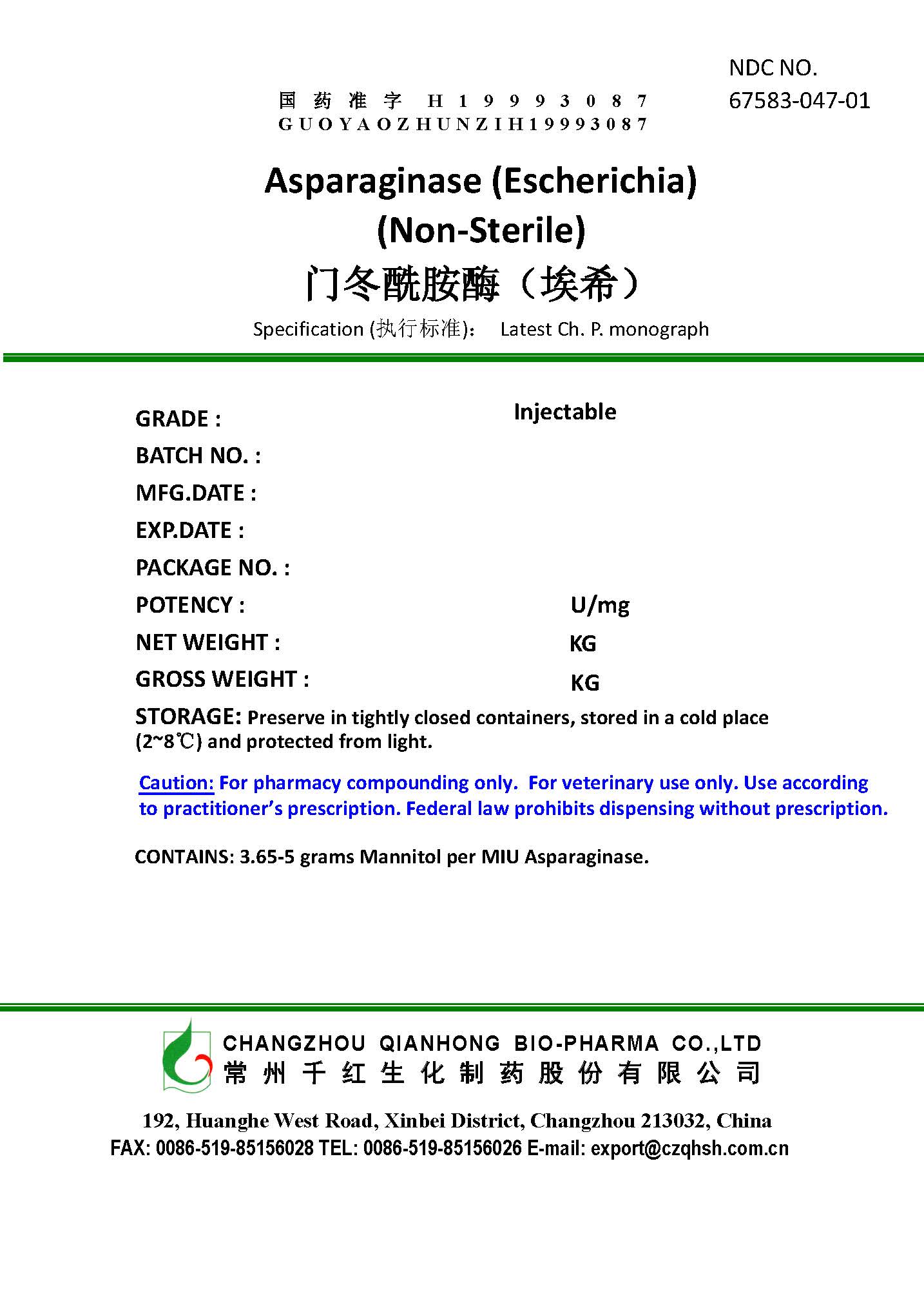 DRUG LABEL: ASPARAGINASE (ESCHERICHIA)
NDC: 67583-047 | Form: POWDER
Manufacturer: Changzhou Qianhong Bio-Pharma Co., Ltd
Category: other | Type: BULK INGREDIENT - ANIMAL DRUG
Date: 20221027

ACTIVE INGREDIENTS: ASPARAGINASE 1 kg/1 kg

asparaginase (escherichia) Non-sterile